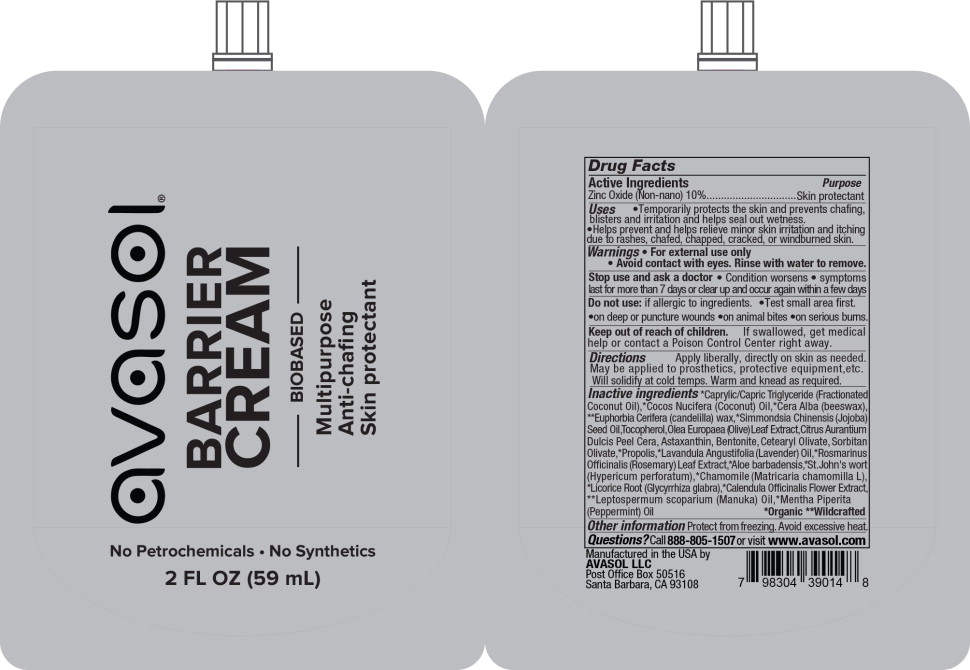 DRUG LABEL: Barrier Cream
NDC: 58518-040 | Form: CREAM
Manufacturer: Avasol LLC
Category: otc | Type: HUMAN OTC DRUG LABEL
Date: 20230515

ACTIVE INGREDIENTS: ZINC OXIDE 100 mg/100 mL
INACTIVE INGREDIENTS: MEDIUM-CHAIN TRIGLYCERIDES; COCONUT OIL; YELLOW WAX; CANDELILLA WAX; JOJOBA OIL; TOCOPHEROL; OLEA EUROPAEA LEAF; ORANGE PEEL WAX; ASTAXANTHIN; BENTONITE; CETEARYL OLIVATE; SORBITAN OLIVATE; PROPOLIS WAX; LAVENDER OIL; ROSEMARY; ALOE VERA WHOLE; ST. JOHN'S WORT; CHAMOMILE; LICORICE; CALENDULA OFFICINALIS FLOWER; MANUKA OIL; PEPPERMINT OIL

Barrier Cream

Active Ingredients

Zinc Oxide (Non-nano) 10%

Purpose

Skin protectant

Uses

- Temporarily protects the skin and prevents chafing, blisters and irritation and helps seal out wetness.
- Helps prevent and helps relieve minor skin irritation and itching due to rashes, chafed, chapped, cracked, or windburned skin.

Warnings

- For external use only
- Avoid contact with eyes. Rinse with water to remove.

Stop use and ask a doctor

- Condition worsens
- symptoms last for more than 7 days or clear up and occur again within a few days

Do not use:

- if allergic to ingredients.
- on deep or puncture wounds
- on animal bites •on serious burns.
- Test small area first.

Keep out of reach of children.

If swallowed, get medical help or contact a Poison Control Center right away.

Directions

Apply liberally, directly on skin as needed. Safe to apply to prosthetics, protective equipment, etc.

Inactive ingredients

*Caprylic/Capric Triglyceride (Fractionated Coconut Oil), *Cocos Nucifera (Coconut) Oil, *Cera Alba (beeswax), **Euphorbia Cerifera (candelilla) wax, *Simmondsia Chinensis (Jojoba) Seed Oil, Tocopherol, Olea Europaea (Olive) Leaf Extract, Citrus Aurantium Dulcis Peel Cera, Astaxanthin, Bentonite, Cetearyl Olivate, Sorbitan Olivate, *Propolis, *Lavandula Angustifolia (Lavender) Oil, *Rosmarinus Officinalis (Rosemary) Leaf Extract,*Aloe barbadensis,*St. John's wort (Hypericum perforatum),*Chamomile (Matricaria chamomilla L), *Licorice Root (Glycyrrhiza glabra), *Calendula Officinalis Flower Extract, **Leptospermum scoparium (Manuka) Oil, *Mentha Piperita (Peppermint) Oil *Organic

Other information

store product between 45 to 100F

Gently warm or knead product as needed to soften before use.

Questions?

Call 888-805-1507 or visit www.avasol.com